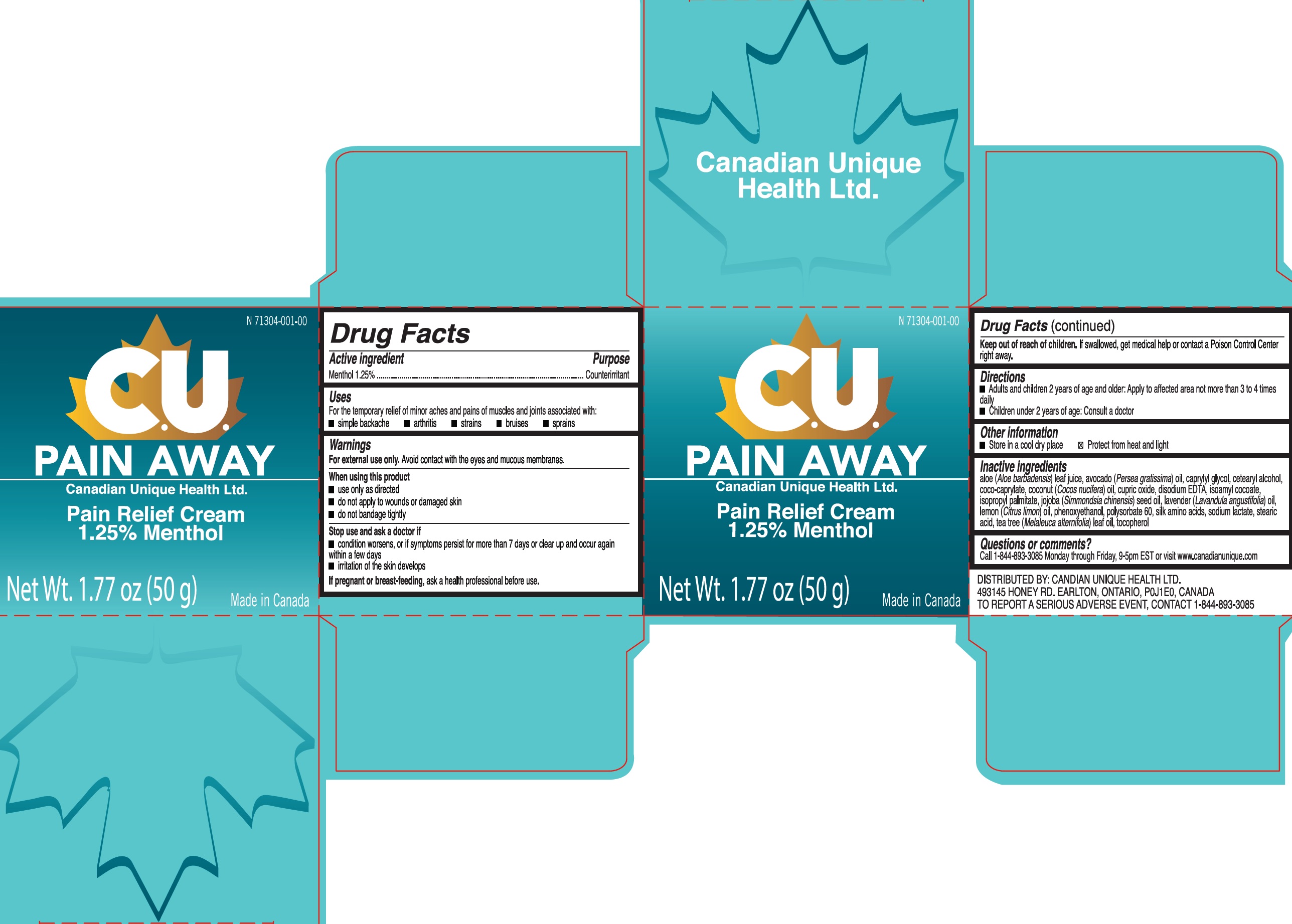 DRUG LABEL: CU Pain Away Pain Relief
NDC: 71304-001 | Form: CREAM
Manufacturer: Canadian Unique Health Ltd.
Category: otc | Type: HUMAN OTC DRUG LABEL
Date: 20250718

ACTIVE INGREDIENTS: MENTHOL 12.5 mg/1 g
INACTIVE INGREDIENTS: ALOE; AVOCADO OIL; CAPRYLYL GLYCOL; CETOSTEARYL ALCOHOL; COCO-CAPRYLATE; COCONUT OIL; CUPRIC OXIDE; EDETATE DISODIUM ANHYDROUS; ISOAMYL COCOATE; ISOPROPYL PALMITATE; JOJOBA OIL; LAVENDER OIL; LEMON OIL; PHENOXYETHANOL; POLYSORBATE 60; AMINO ACIDS, SILK; SODIUM LACTATE; STEARIC ACID; TOCOPHEROL

CU Pain Away Pain Relief

Active ingredient

Menthol 1.25%

Purpose

Counterirritant

Uses

For the temporary relief of minor aches and pains of muscles and joints associated with:

- simple backache
- arthritis
- strains
- bruises
- sprains

Warnings

For external use only. Avoid contact with the eyes and mucous membranes.

When using this product

- use only as directed
- do not apply to wounds or damaged skin
- do not bandage tightly

Stop use and ask a doctor if

- condition worsens, or if symptoms persist for more than 7 days or clear up and occur again within a few days
- irritation of the skin develops If pregnant or breast-feeding, ask a health professional before use.

Keep out of reach of children.

If swallowed, get medical help or contact a Poison Control Center right away.

Directions

- Adults and children 2 years of age and older: Apply to affected area not more than 3 to 4 times daily
- Children under 2 years of age: Consult a doctor

Other information

- Store in a cool dry place
- Protect from heat and light

Inactive ingredients

aloe (Aloe barbadensis) leaf juice, avocado (Persea gratissima) oil, caprylyl glycol, cetearyl alcohol, coco-caprylate, coconut (Cocos nucifera) oil, cupric oxide, disodium EDTA, isoamyl cocoate, isopropyl palmitate, jojoba (Simmondsia chinensis) seed oil, lavender (Lavandula angustifolia) oil, lemon (Citrus limon) oil, phenoxyethanol, polysorbate 60, silk amino acids, sodium lactate, stearic acid, tea tree (Melaleuca alternifolia) leaf oil, tocopherol

Questions or comments?

Call 1-844-893-3085 Monday through Friday, 9-5pm EST or visit www.canadianunique.com